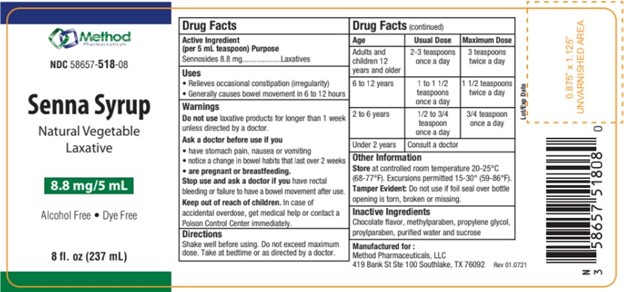 DRUG LABEL: Senna Syrup
NDC: 58657-518 | Form: LIQUID
Manufacturer: Method Pharmaceuticals
Category: otc | Type: HUMAN OTC DRUG LABEL
Date: 20251021

ACTIVE INGREDIENTS: SENNOSIDES 8.8 mg/5 mL
INACTIVE INGREDIENTS: WATER; PROPYLENE GLYCOL; SUCROSE; METHYLPARABEN; PROPYLPARABEN

Senna Syrup

Active Ingredients

Sennosides 8.8 mg

Purpose

Laxative

Warning

Do not use laxative products for longer than 1 week
unless directed by a doctor.

Uses

• Relieves occasional constipation (irregularity)
• Generally causes bowel movement in 6 to 12 hours

Ask a doctor before use if you

• have stomach pain, nausea or vomiting
• notice a change in bowel habits that last over 2 weeks
• are pregnant or breastfeeding.

Stop Use and ask a doctor

if you have rectal bleeding or failure to have a bowel movement after use.

Keep out of Reach of Children

In case of accidental overdose, get medical help or contact a Poison Control Center immediately.

Directions

Shake well before using. Do not exceed maximum dose. Take at bedtime or as directed by a doctor.

OTHER SAFETY INFORMATION

Store at controlled room temperature 20-25°C(68-77°F). Excursions permitted 15-30° (59-86°F).
Tamper Evident: Do not use if foil seal over bottle opening is torn, broken or missing.

Inactive Ingredients

Chocolate flavor, methylparaben, propylene glycol, proylparaben, purified water and sucrose

Dosage

Age | Usual Dose | Maximum Dose
Adults and Children 12 years and older | 2-3 teaspoons once a day | 3 teaspoons twice a day
6-12 years | 1 to 1 1/2 teaspoons once a day | 1 1/2 teaspoons twice a day
2-6 years | 1/2 to 3/4 teaspoon once a day | 3/4 teaspoons twice a day
under 2 years | Consult a doctor

Senna Syrup

Manufactured for :
Method Pharmaceuticals, LLC
419 Bank St Ste 100 Southlake, TX 76092

Rev 01.0721